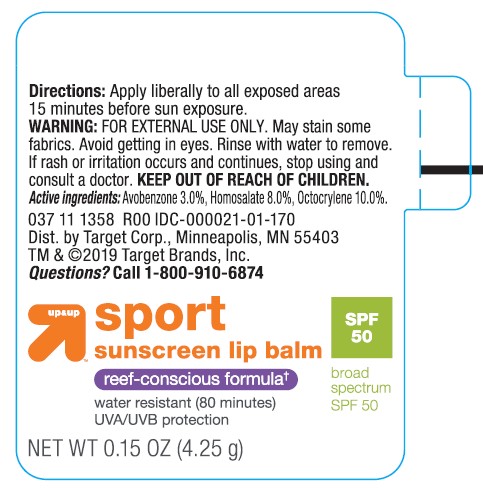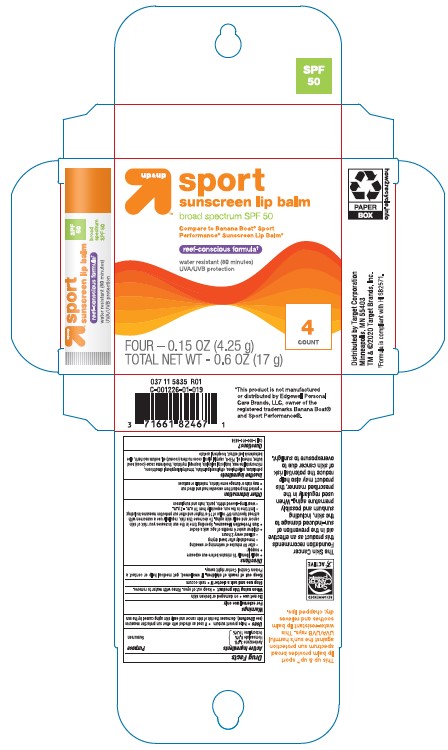 DRUG LABEL: Target Up and Up SPF50 Sport Sunscreen Lip Balm Reef-Conscious Formula
NDC: 11673-168 | Form: STICK
Manufacturer: TARGET CORPORATION
Category: otc | Type: HUMAN OTC DRUG LABEL
Date: 20241014

ACTIVE INGREDIENTS: HOMOSALATE 80 mg/1 g; OCTOCRYLENE 100 mg/1 g; AVOBENZONE 30 mg/1 g
INACTIVE INGREDIENTS: MINERAL OIL; POLYETHYLENE GLYCOL 400; PETROLATUM; SACCHARIN SODIUM ANHYDROUS; COCONUT OIL; HIGH DENSITY POLYETHYLENE; CAPRYLYL GLYCOL; ETHYLHEXYL PALMITATE; .ALPHA.-TOCOPHEROL ACETATE; COCOA BUTTER; BUTYLOCTYL SALICYLATE; ALOE VERA LEAF; ISOPROPYL MYRISTATE; MICROCRYSTALLINE WAX

Target Up & Up SPF50 Sport Sunscreen Lip Balm Reef-Conscious Formula

Active ingredients

Avobenzone 3.0%

Homosalate 8.0%

Octocrylene 10.0%

Purpose

Sunscreen

Uses

• helps prevent sunburn • if used as directed with other sun protection measures (see Directions), decreases the risk of skin cancer and early skin aging caused by the sun

Warnings

For external use only

Do not use

•on damaged or broken skin.

When using this product

• keep out of eyes. Rinse with water to remove.

Stop use and ask a doctor if

• rash occurs.

Keep out of reach of children

If product is swallowed, get medical help or contact a Poison Control Poison Control Center right away.

Directions

• apply liberally 15 minutes before sun exposure

• reapply:

• after 80 minutes of swimming or sweating

• immediately after towel drying

• at least every 2 hours

• children under 6 months of age: Ask a doctor

• Sun Protection Measures. Spending time in the sun increases your risk of skin cancer and early skin aging. To decrease this risk, regularly use a sunscreen with a Broad Spectrum SPF value of 15 or higher and other sun protection measures including:

• limit time in the sun, especially from 10 a.m. - 2 p.m.

• wear long-sleeved shirts, pants, hats, and sunglasses

Other information

• protect the product in this container from excessive heat and direct sun

• may stain or damage some fabrics, materials, or surfaces

Inactive ingredients

Petrolatum, Polyethylene, Ethylhexyl Palmitate, Trimethylsiloxyphenyl Dimethicone, Microcrystalline Wax, Butyloctyl Salicylate, Isopropyl Myristate, Theobroma Cacao (Cocoa) Seed Butter, Mineral Oil, PEG-8, Caprylyl Glycol, Cocos Nucifera (Coconut) Oil, Sodium Saccharin, Aloe Barbadensis Leaf Extract, Tocopheryl Acetate.